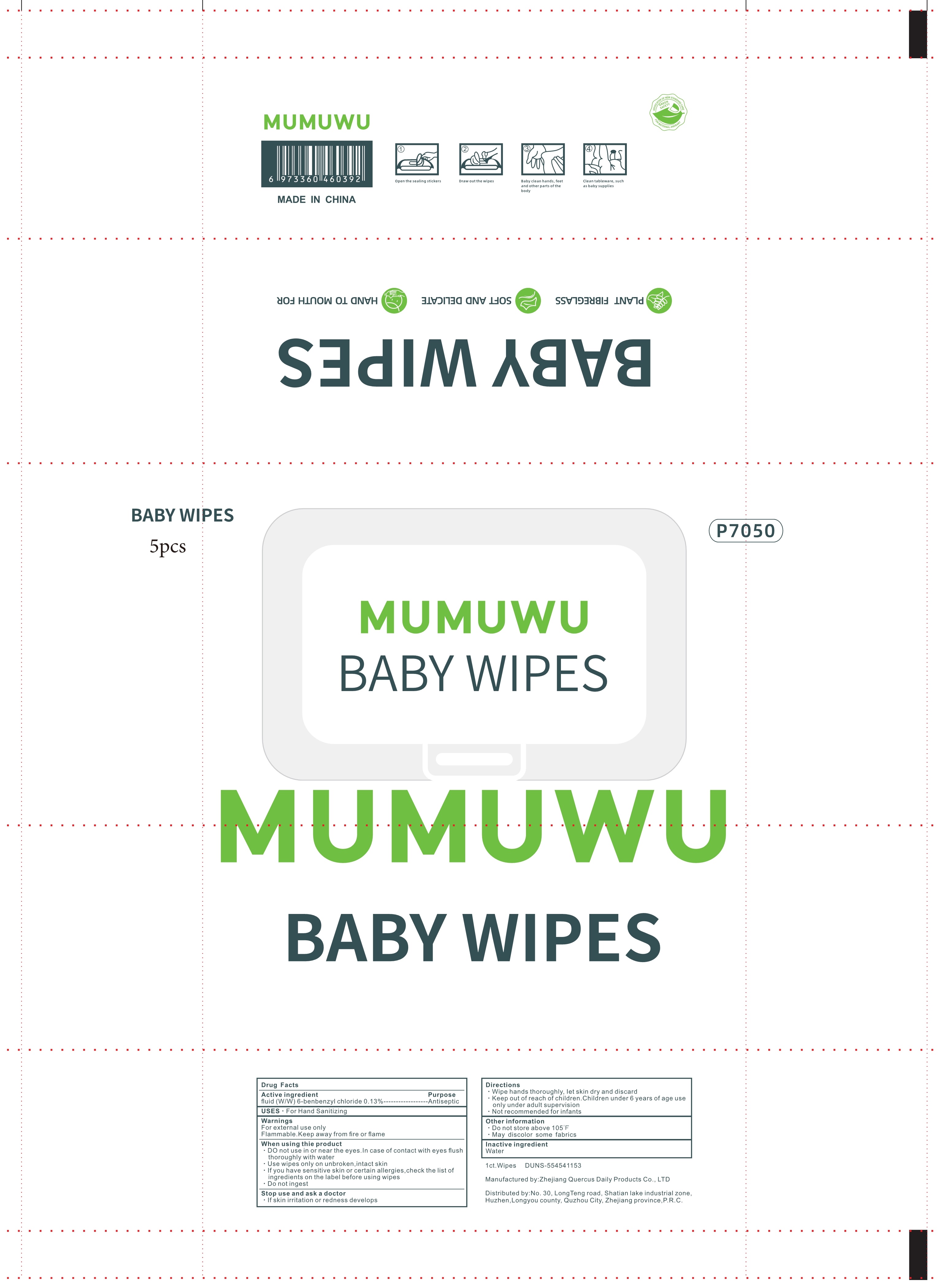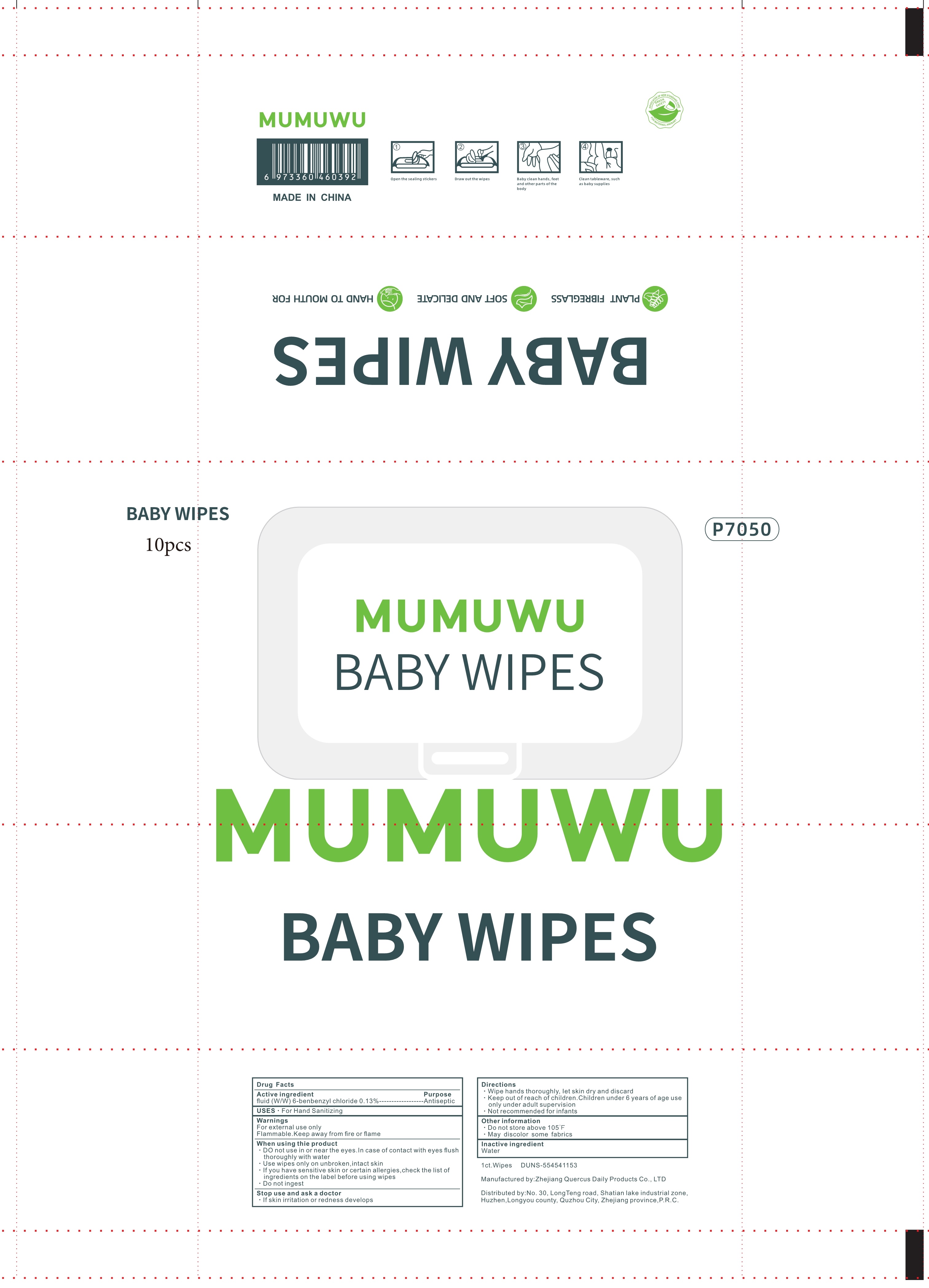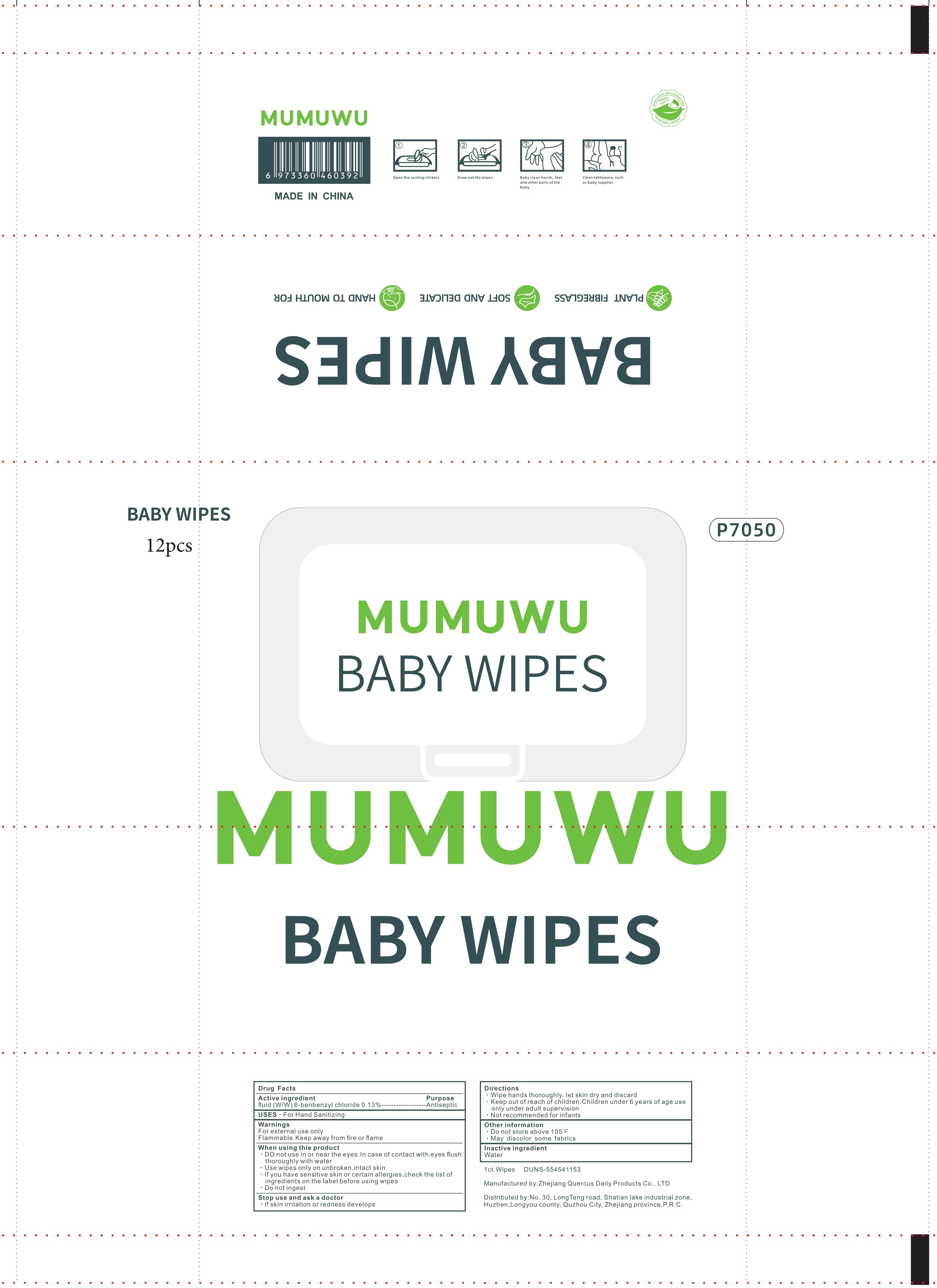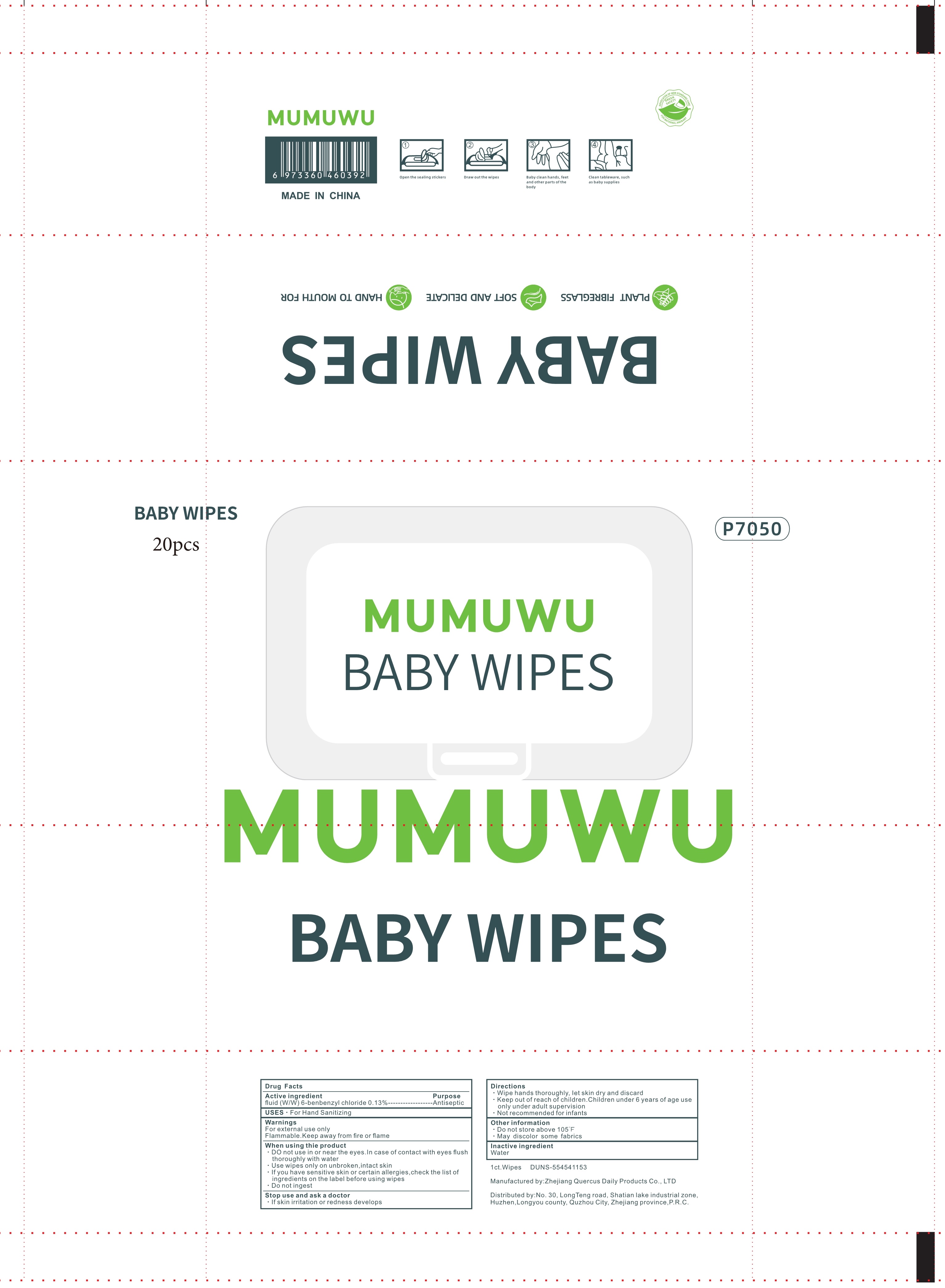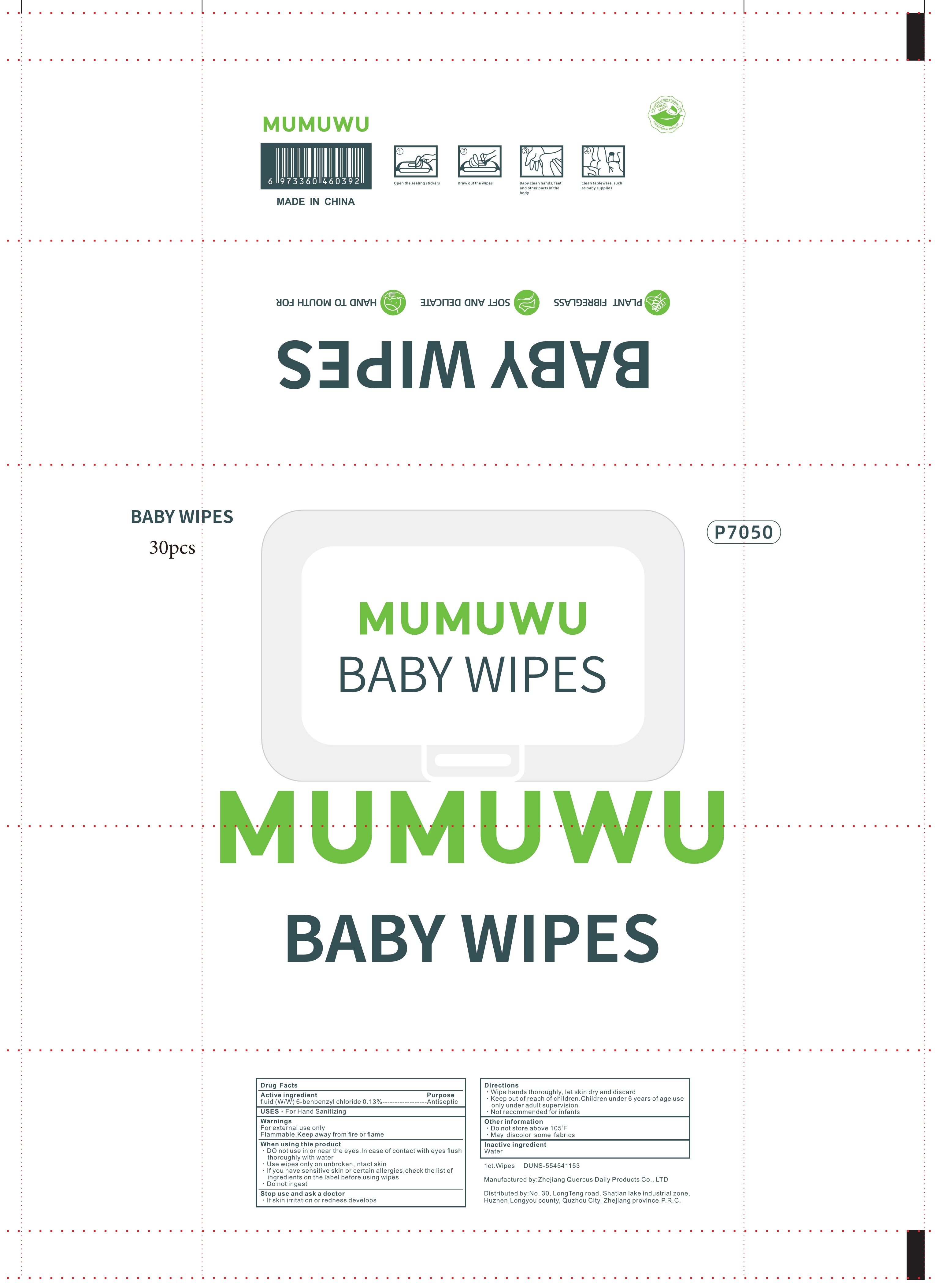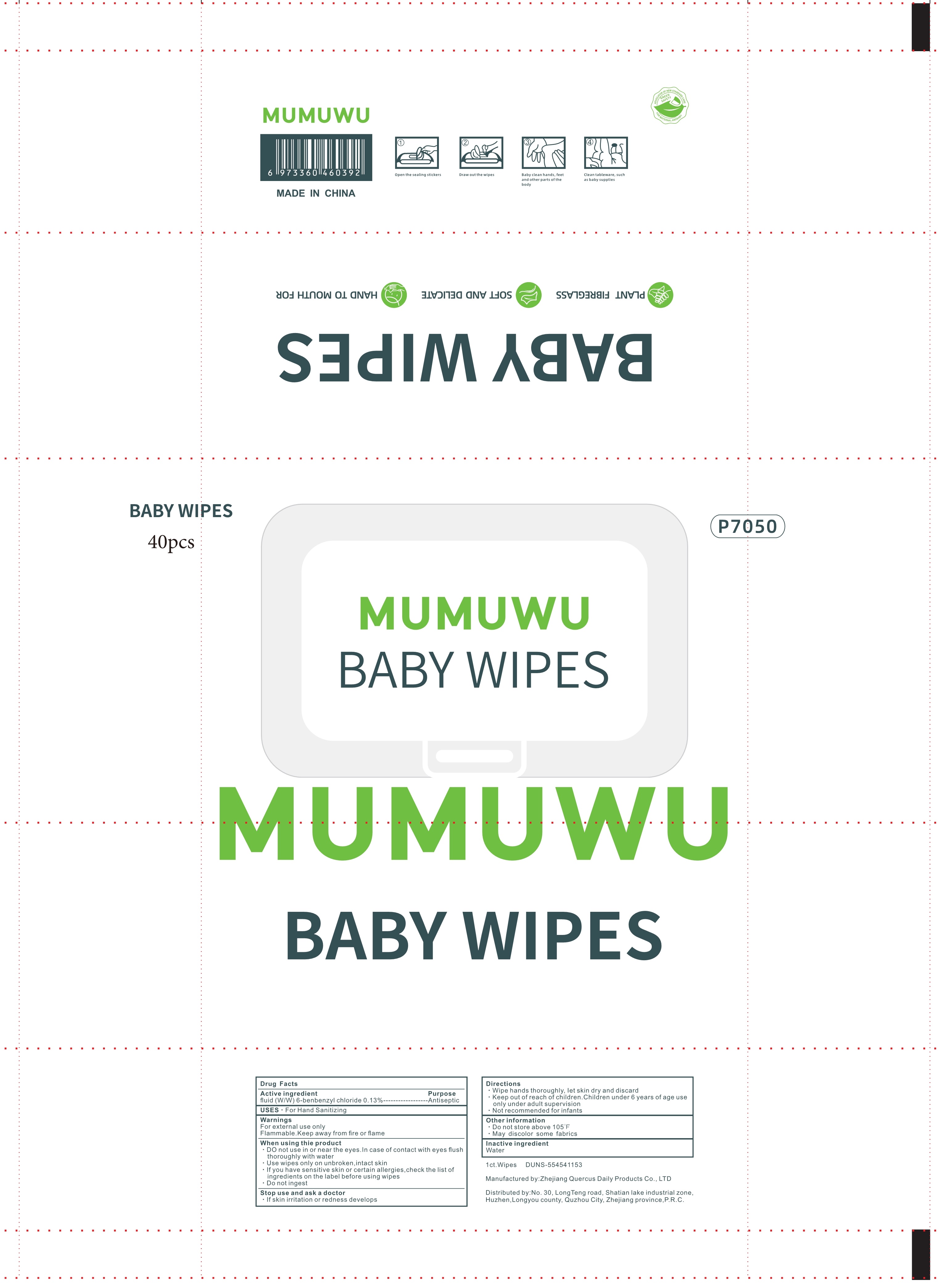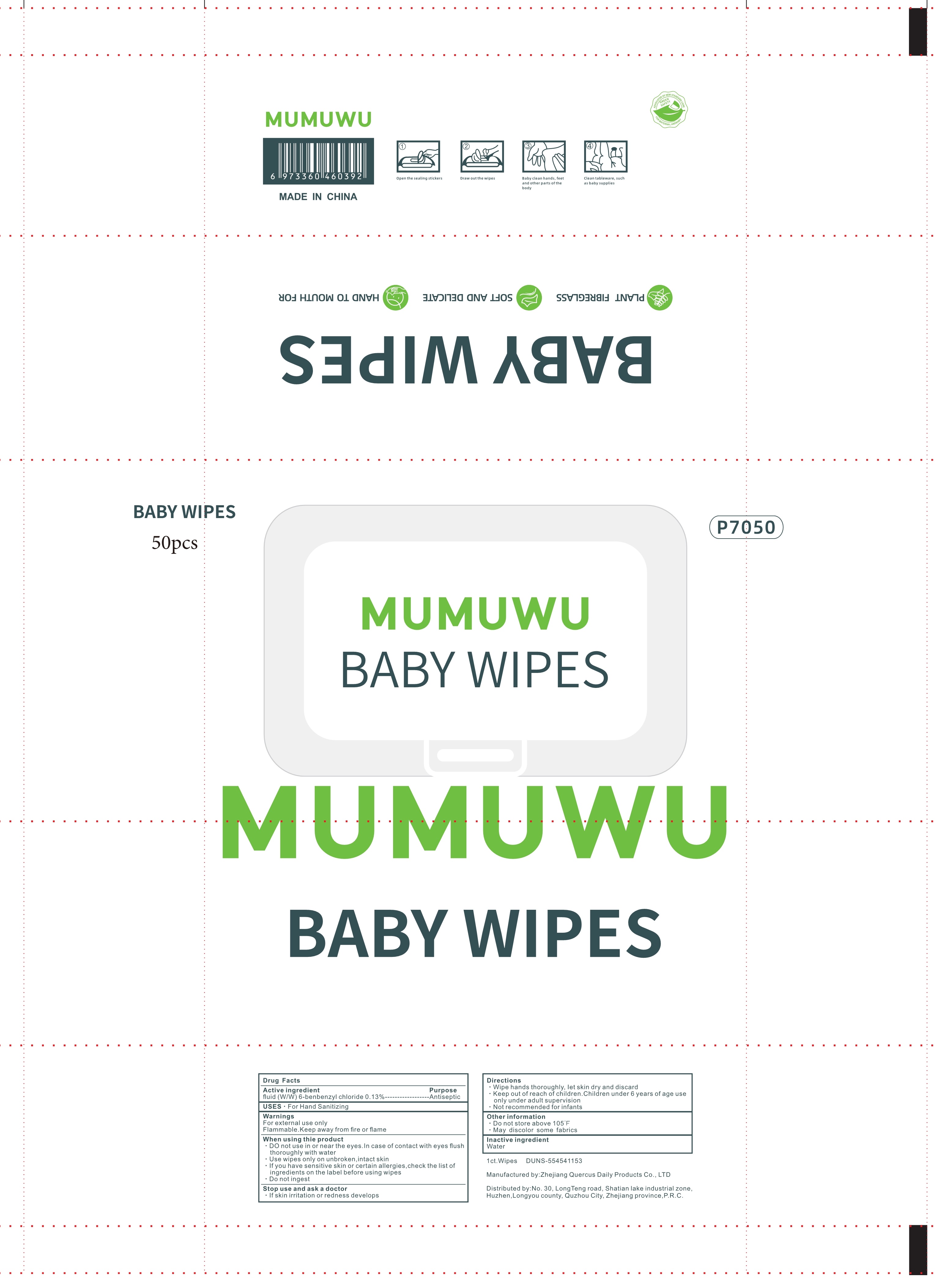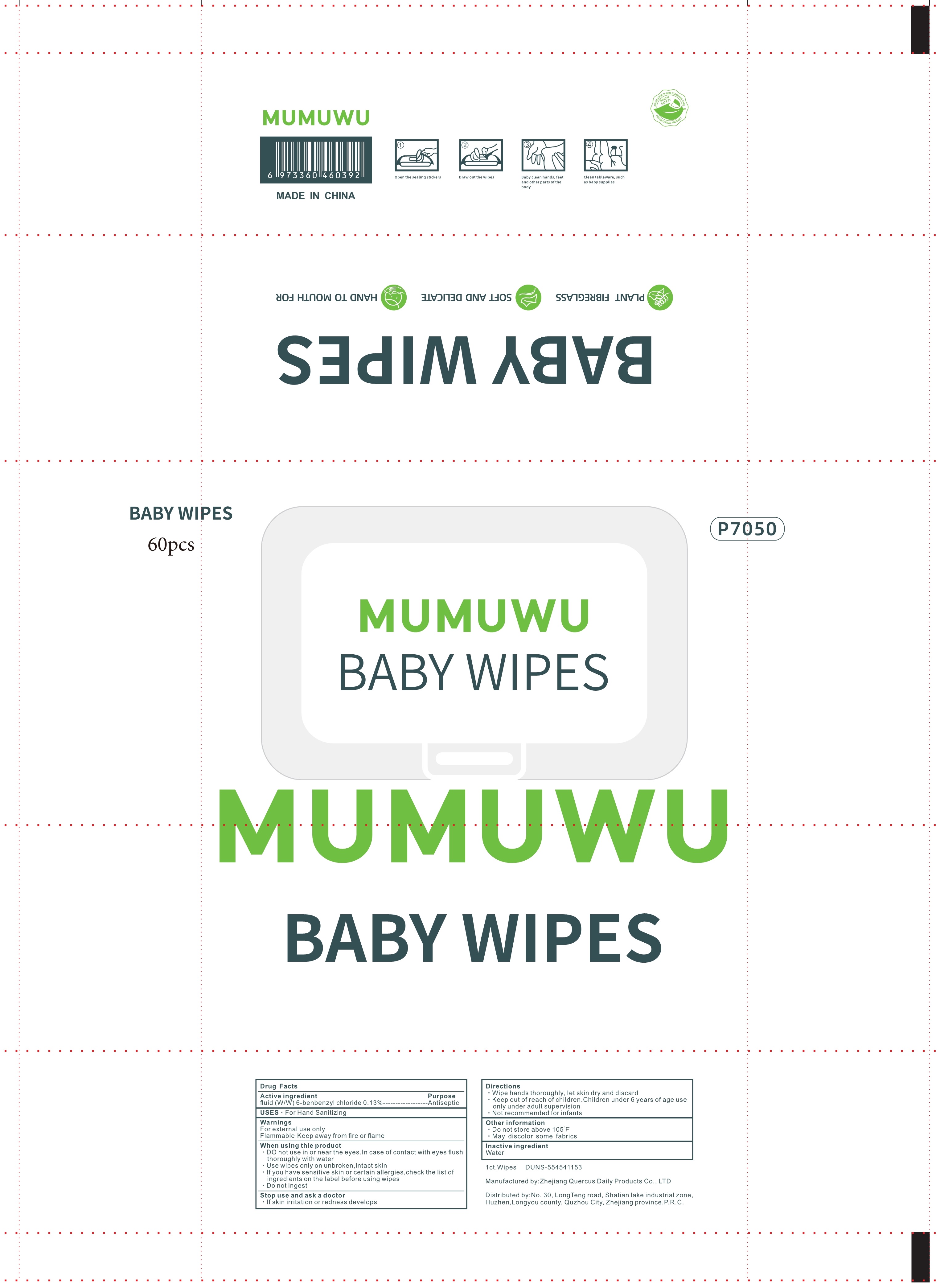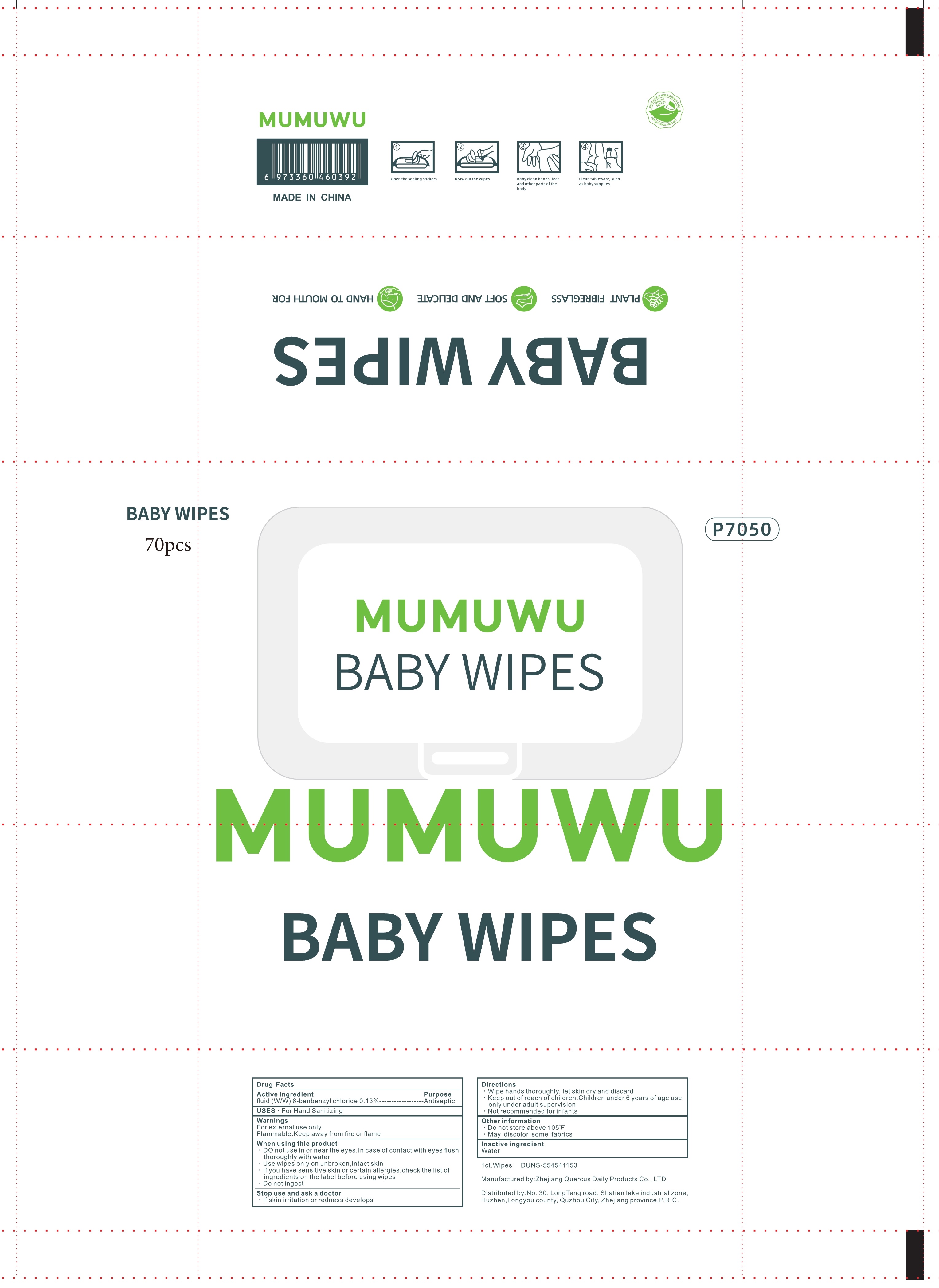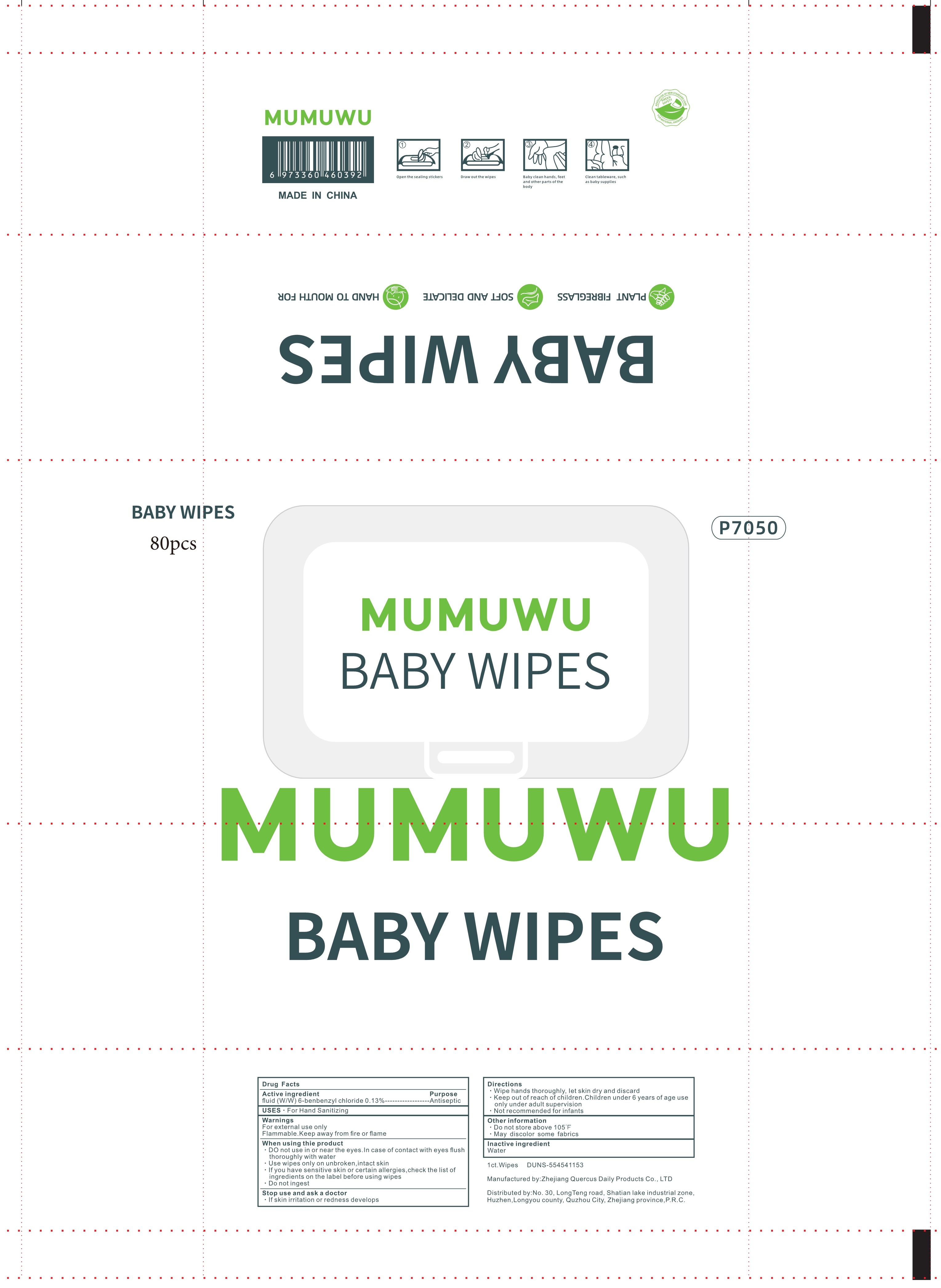 DRUG LABEL: Baby hand and mouth wipes
NDC: 90017-003 | Form: CLOTH
Manufacturer: Zhejiang quercus daily necessities Co., Ltd
Category: otc | Type: HUMAN OTC DRUG LABEL
Date: 20201230

ACTIVE INGREDIENTS: BENZALKONIUM CHLORIDE 0.13 g/100 1
INACTIVE INGREDIENTS: WATER

90017-003
Baby hand and mouth wipes

Active Ingredient(s)

fluid (W/W) 6-benbenzyl chloride 0.13%

Purpose

Antiseptic

Use

For Hand Sanitizing

Warnings

For external use only
Flammable.Keep away from fire or flame

- ·DO not use in or near the eyes.In case of contact with eyes flush thoroughly with water

·DO not use in or near the eyes.In case of contact with eyes flush thoroughly with water
·Use wipes only on unbroken,intact skin
·If you have sensitive skin or certain allergies,check the list of ingredients on the label before using wipes
·Do not ingest

Stop use and ask a doctor
·If skin irritation or redness develops

·Keep out of reach of children.Children under 6 years of age use only under adult supervision

Directions

·Wipe hands thoroughly, Iet skin dry and discard
·Keep out of reach of children.Children under 6 years of age use only under adult supervision
·Not recommended for infants

Other information

·Do not store above 105℉
·May discolor some fabrics

Inactive ingredients

Water

Package Label - Principal Display Panel

90017-003-01 5pcs

90017-003-02 10pcs

90017-003-03 12pcs

90017-003-04 20pcs

90017-003-05 30pcs

90017-003-06 40pcs

90017-003-07 50pcs

90017-003-08 60pcs

90017-003-09 70pcs

90017-003-10 80pcs